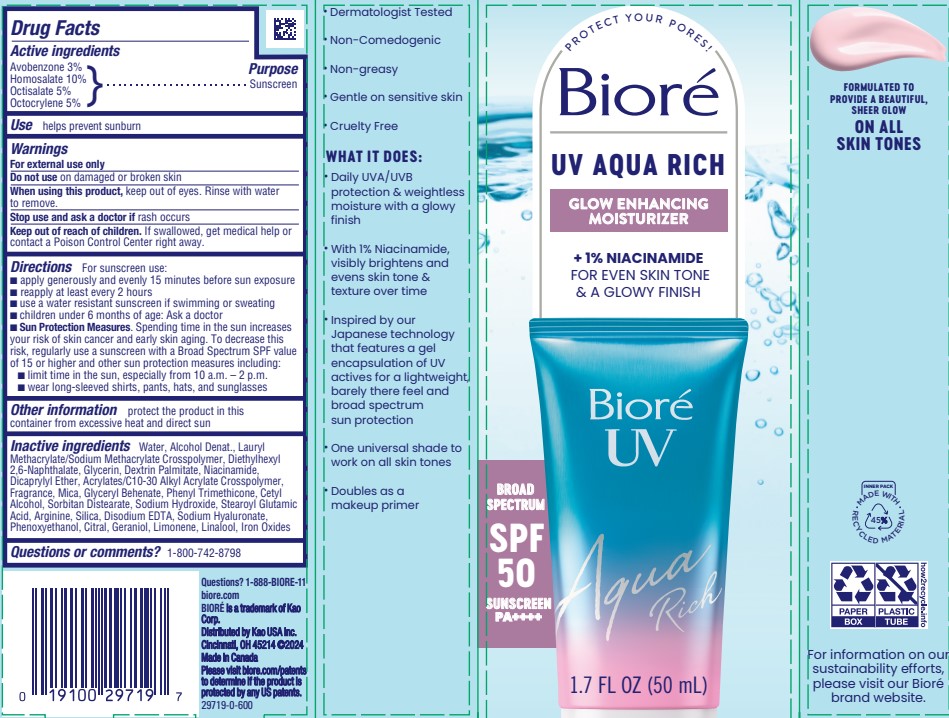 DRUG LABEL: Biore UV Aqua Rich
NDC: 10596-198 | Form: LIQUID
Manufacturer: KAO USA
Category: otc | Type: HUMAN OTC DRUG LABEL
Date: 20250115

ACTIVE INGREDIENTS: OCTISALATE 5 g/100 mL; OCTOCRYLENE 5 g/100 mL; HOMOSALATE 10 g/100 mL; AVOBENZONE 3 g/100 mL
INACTIVE INGREDIENTS: CARBOMER COPOLYMER TYPE A (ALLYL PENTAERYTHRITOL CROSSLINKED); LAURYL METHACRYLATE; DIETHYLHEXYL 2,6-NAPHTHALATE; GLYCERIN; DICAPRYLYL ETHER; ARGININE; CETYL ALCOHOL; CITRAL; GLYCERYL DIBEHENATE; PHENYL TRIMETHICONE; EDETATE DISODIUM; GERANIOL; WATER; ALCOHOL; DEXTRIN PALMITATE (CORN; 20000 MW); NIACINAMIDE; SILICON DIOXIDE; PHENOXYETHANOL; SODIUM HYDROXIDE; LIMONENE, (+)-; LINALOOL; MICA; SORBITAN DISTEARATE; STEAROYL GLUTAMIC ACID; IRON OXIDES; SODIUM HYALURONATE

Biore UV Aqua Rich

Active ingredients

Avobenzone 3%

Homosalate 10%

Octisalate 5%

Octocrylene 5%

Purpose

Sunscreen

INDICATIONS AND USAGE

Use helps prevent sunburn

Warnings

For external use only

Do not use on damaged or broken skin

When using this product, keep out of eyes. Rinse with water to remove.

Stop use and ask a doctor if rash occurs

Keep out of reach of children. If swallowed, get medical help or contact a Poison Cotrol Center right away.

DOSAGE AND ADMINISTRATION

Directions For sunscreen use:

- apply generously and evenly 15 minutes before sun exposure
- reapply at least every 2 hours
- use a water resistant sunscreen if swimming or sweating
- children under 6 months of age: Ask a doctor
- Sun Protection Measures. Spending time in the sun increases your risk of skin cancer and early skin aging. To decrease this risk, regularly use a sunscreen with a Broad Spectrum SPF value of 15 or higher and other sun protection measures including:

• limit time in the sun, especially from 10 a.m. - 2 p.m.

• wear long-sleeved shirts, pants, hats, and sunglasses

Other information

protect the product in this container from excessive heat and direct sun

INACTIVE INGREDIENT

Inactive ingredients Water, Alcohol Denat., Lauryl Methacrylate/Sodium Methacxrylate Crosspolymer, Diethylhexyl 2,6-Naphthalate, Glyerin, Dextrin Palmitate, Niacinamide, Dicaprylyl Ether, Acrylates/C10-30 Alkyl Acrylate Crosspolymer, Fragrance, Mica, Glyceryl Behenate, Phyl Trimethicone, Cetyl Alcohol, Sorbitan Distearate, Sodium Hydroxide, Stearoyl Glutamic Acid, Arginine, Silica, Disodium EDTA, Sodium Hyaluronate, Phenoxyethanol, Citral, Geraniol, Limonene, Linalool, Iron Oxides

Questions or comments? 1-800-742-8798

Questions? 1-888-BIORE-11

biore.com

BIORE is a trademark of Kao Corp.

Distributed by Kao USA Inc.

Cincinnati, OH 45214 ©2024

Made in Canada

PACKAGE LABEL

Biore

US AQUA RICH

Glow Enhancing Moisturizer

+1% NIACINAMIDE

FOR EVEN SKIN TONE & A GLOWY FINISH

Biore UV

Aqua Rich

BROAD SPECTRUM

SPF 50

SUNSCREEN

PA++++

1.7 FL OZ (50 mL)